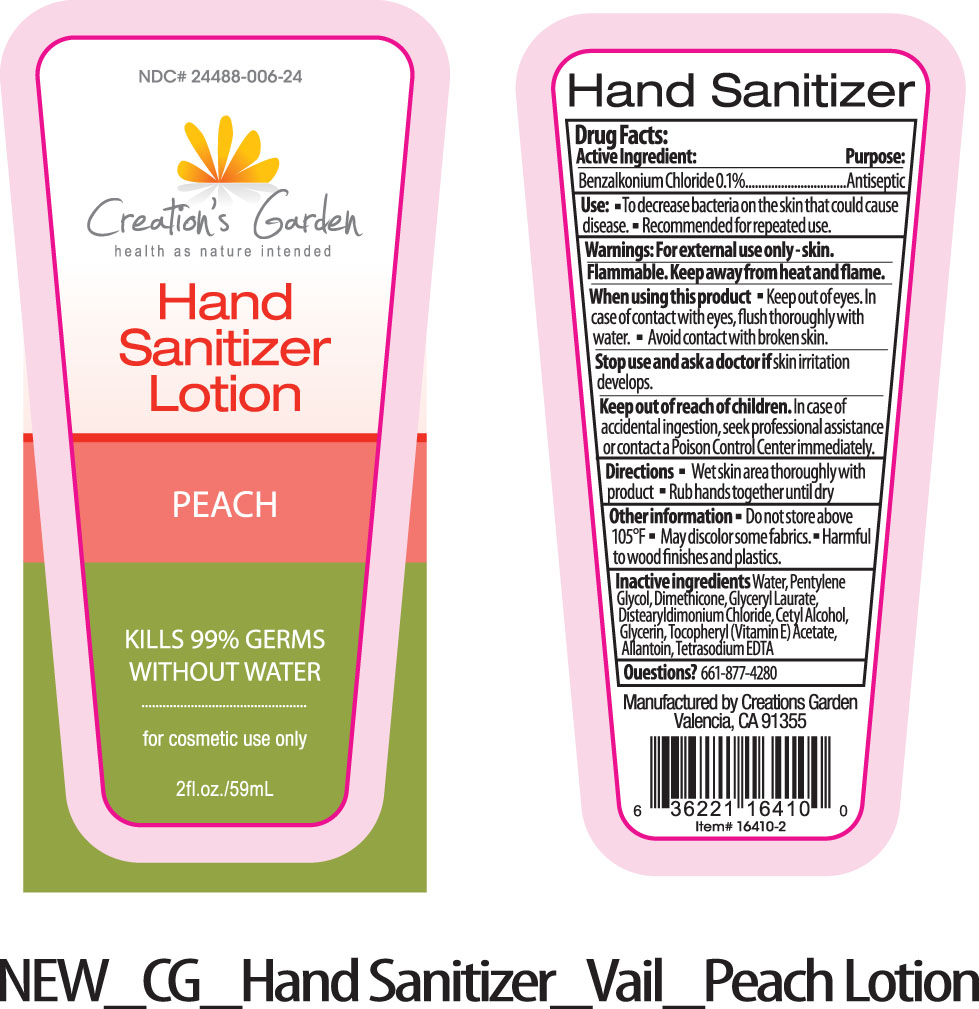 DRUG LABEL: Creations Garden
NDC: 24488-006 | Form: LOTION
Manufacturer: Creations Garden Natural Products
Category: otc | Type: HUMAN OTC DRUG LABEL
Date: 20110504

ACTIVE INGREDIENTS: BENZALKONIUM CHLORIDE 0.59 mL/59 mL
INACTIVE INGREDIENTS: WATER; PENTYLENE GLYCOL; DIMETHICONE; GLYCERYL LAURATE; DISTEARYLDIMONIUM CHLORIDE; CETYL ALCOHOL; GLYCERIN; ALPHA-TOCOPHEROL ACETATE; ALLANTOIN; EDETATE SODIUM

Drug Facts:

Active Ingredient:.................................Purpose:

Benzalkonium Chloride 0.1%.................................Antiseptic

Use:

- To decrease bacteria on the skin that could cause disease.
- Recommended for repeated use.

Warnings:

For external use only-skin.

Flammable. Keep away from heat and flame.

When using this product:

- Keep out of eyes. In case of contact with eyes, flush thoroughly with water
- Avoid contact with broken skin.

Stop use and ask a doctor if

skin irritation develops.

Keep out of reach of children.

In case of accidental ingestion, seek professional assistance or contact a Poison Control Center immediately.

Directions:

- Wet skin area thoroughly with product
- Rub hands together until dry

Other information:

- Do not store above 105°.
- May discolor some fabrics.
- Harmful to wood finishes and plastics.

Inactive ingredients:

Water, Pentylene Glycol, Dimethicone, Glyceryl Laurate, Distearyldimondium Chloride, Cetyl Alcohol, Glycerin, Tocopheryl (Vitamin E) Acetate, Allantoin, Tetrasodium EDTA

Questions?

661-877-4280

PACKAGE LABEL

Placeholder Text